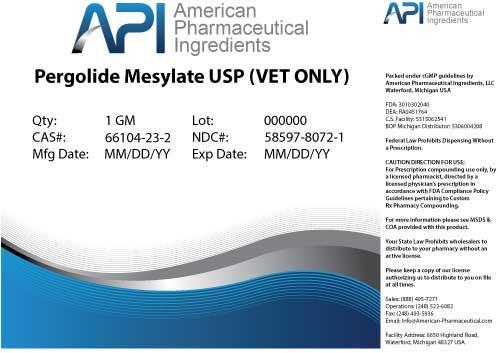 DRUG LABEL: Pergolide Mesylate
NDC: 58597-8072 | Form: POWDER
Manufacturer: AMERICAN PHARMACEUTICAL INGREDIENTS LLC
Category: other | Type: BULK INGREDIENT
Date: 20140416

ACTIVE INGREDIENTS: Pergolide Mesylate 1 g/1 g

Pergolide Mesylate